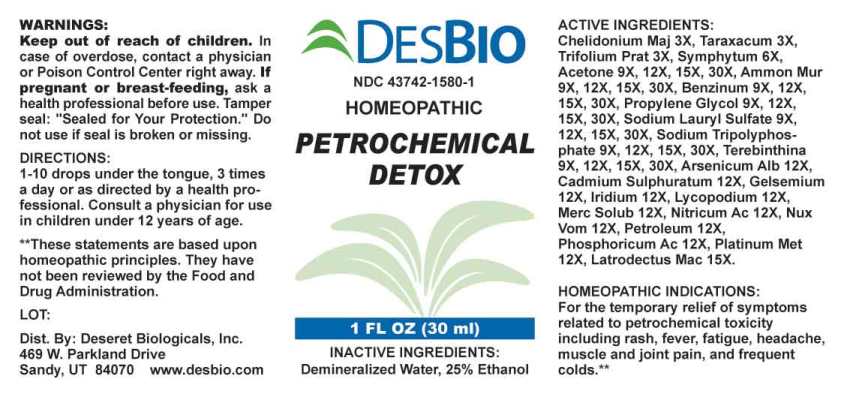 DRUG LABEL: Petrochemical Detox
NDC: 43742-1580 | Form: LIQUID
Manufacturer: Deseret Biologicals, Inc.
Category: homeopathic | Type: HUMAN OTC DRUG LABEL
Date: 20230112

ACTIVE INGREDIENTS: CHELIDONIUM MAJUS 3 [hp_X]/1 mL; TARAXACUM OFFICINALE 3 [hp_X]/1 mL; TRIFOLIUM PRATENSE FLOWER 3 [hp_X]/1 mL; COMFREY ROOT 6 [hp_X]/1 mL; ACETONE 9 [hp_X]/1 mL; AMMONIUM CHLORIDE 12 [hp_X]/1 mL; PROPYLENE GLYCOL 12 [hp_X]/1 mL; BENZENE 12 [hp_X]/1 mL; SODIUM LAURYL SULFATE 12 [hp_X]/1 mL; SODIUM TRIPOLYPHOSPHATE 12 [hp_X]/1 mL; TURPENTINE OIL 12 [hp_X]/1 mL; ARSENIC TRIOXIDE 12 [hp_X]/1 mL; CADMIUM SULFIDE 12 [hp_X]/1 mL; GELSEMIUM SEMPERVIRENS ROOT 12 [hp_X]/1 mL; IRIDIUM 12 [hp_X]/1 mL; LYCOPODIUM CLAVATUM SPORE 12 [hp_X]/1 mL; MERCURIUS SOLUBILIS 12 [hp_X]/1 mL; NITRIC ACID 12 [hp_X]/1 mL; STRYCHNOS NUX-VOMICA SEED 12 [hp_X]/1 mL; KEROSENE 12 [hp_X]/1 mL; PHOSPHORIC ACID 12 [hp_X]/1 mL; PLATINUM 12 [hp_X]/1 mL; LATRODECTUS MACTANS 15 [hp_X]/1 mL
INACTIVE INGREDIENTS: WATER; ALCOHOL

Drug Facts:

ACTIVE INGREDIENTS:

Chelidonium Majus 3X, Taraxacum Officinale 3X, Trifolium Pratense 3X, Symphytum Officinale 3X, Acetone 9X, 12X, 15X, 30X, Sodium Tripolyphosphate 9X, 12X, 15X, 30X, Propylene Glycol 9X, 12X, 15X, 30X, Benzinum 9X, 12X, 15X, 30X, Ammonium Muriaticum 9X, 12X, 15X, 30X, Sodium Lauryl Sulfate 9X, 12X, 15X, 30X, Terebinthina 9X, 12X, 15X, 30X, Arsenicum Album 12X, Cadmium Sulphuratum 12X, Gelsemium Sempervirens 12X, Iridium Metallicum 12X, Lycopodium Clavatum 12X, Mercurius Solubilis 12X, Nitricum Acidum 12X, Nux Vomica 12X, Petroleum 12X, Phosphoricum Acidum 12X, Platinum Metallicum 12X, Latrodectus Mactans 15X.

HOMEOPATHIC INDICATIONS:

For the temporary relief of symptoms related to petrochemical toxicity including rash, fever, fatigue, headache, muscle and joint pain, and frequent colds.**

**These statements are based upon traditional homeopathic principles. They have not been reviewed by the Food and Drug Administration.

WARNINGS:

Keep out of reach of children. In case of overdose, contact physician or Poison Control Center right away.

If pregnant or breast-feeding, ask a health professional before use.

Tamper seal: "Sealed for Your Protection." Do not use if seal is broken or missing.

Keep out of reach of children. In case of overdose, contact physician or Poison Control Center right away.

DIRECTIONS:

1-10 drops under the tongue, 3 times a day or as directed by a health professional.
Consult a physician for use in children under 12 years of age.

HOMEOPATHIC INDICATIONS:

For the temporary relief of symptoms related to petrochemical toxicity including rash, fever, fatigue, headache, muscle and joint pain, and frequent colds.**
**These statements are based upon traditional homeopathic principles. They have not been reviewed by the Food and Drug Administration.

INACTIVE INGREDIENTS:

Demineralized Water, 25% Ethanol

QUESTIONS:

Dist. By: Deseret Biologicals, Inc.

469 W. Parkland Drive

Sandy, UT 84070 www.desbio.com

*For a complete list of Environmental Isodes contact Deseret Biologicals, Inc.

PACKAGE LABEL DISPLAY:

DESBIO
NDC 43742-1580-1
HOMEOPATHIC
PETROCHEMICAL
DETOX
1 FL OZ (30 ml)